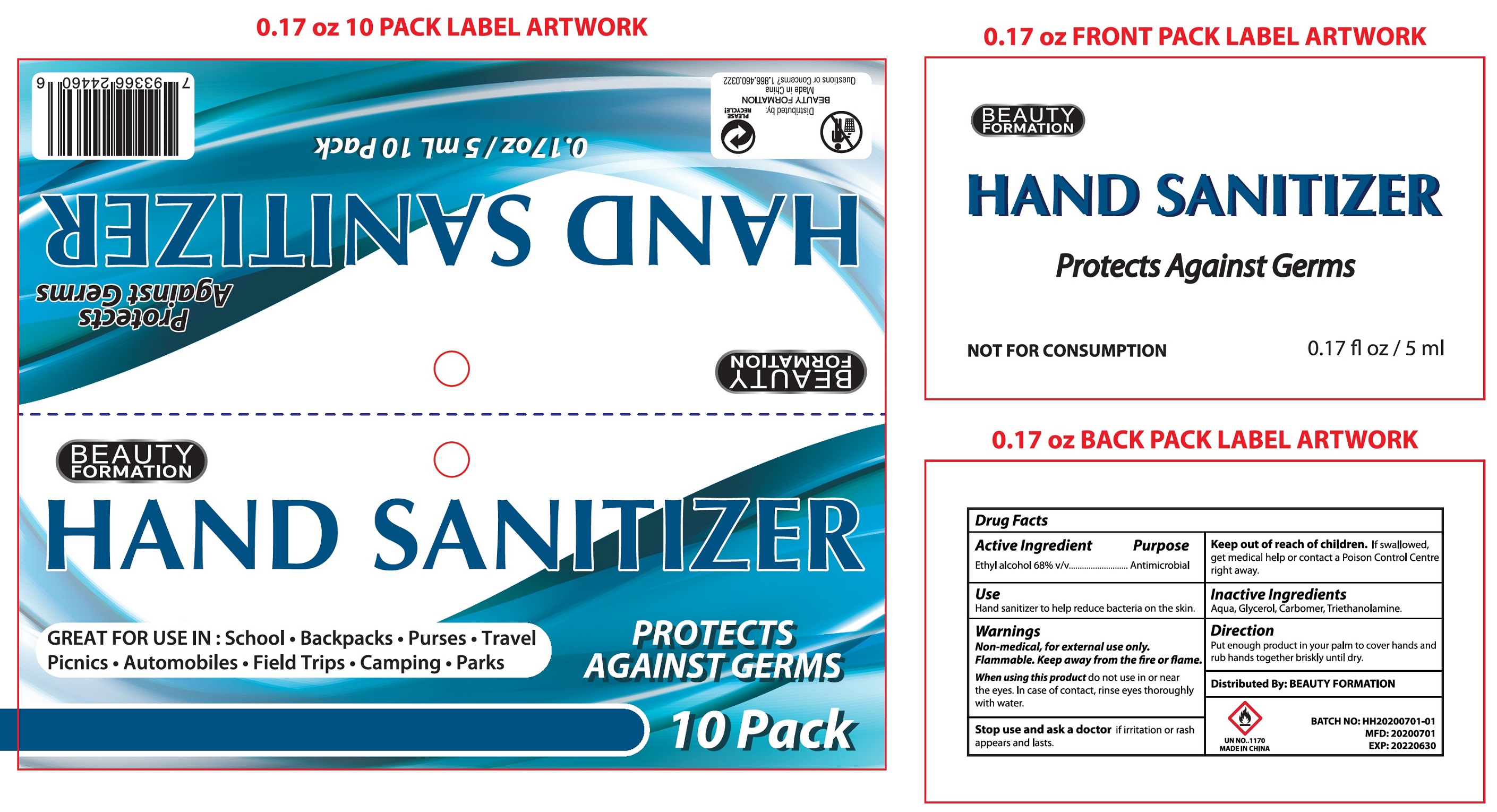 DRUG LABEL: Beauty Formation Hand Sanitizer Individual
NDC: 50435-104 | Form: GEL
Manufacturer: Filo America
Category: otc | Type: HUMAN OTC DRUG LABEL
Date: 20211216

ACTIVE INGREDIENTS: ALCOHOL 0.68 mL/1 mL
INACTIVE INGREDIENTS: WATER; GLYCERIN; CARBOMER HOMOPOLYMER, UNSPECIFIED TYPE; TROLAMINE

Beauty Formation Hand Sanitizer Individual

Active Ingredient

Ethyl alcohol 68% v/v

Purpose

Antimicrobial

Use

Hand sanitizer to help reduce bacteria on the skin.

Warnings

Non-medical, for external use only.

Flammable. Keep away from the fire or flame.

When using this product

do not use in or near the eyes. In case of contact, rinse eyes thoroughly with water.

Stop use and ask a doctor

if irritation or rash appears and lasts.

Keep out of reach of children.

If swallowed, get medical help or contact a Poison Control Centre right away.

Inactive Ingredients

Aqua, Glycerol, Carbomer, Triethanolamine.

Direction

Put enough product in your palm to cover hands and rub hands together briskly until dry.